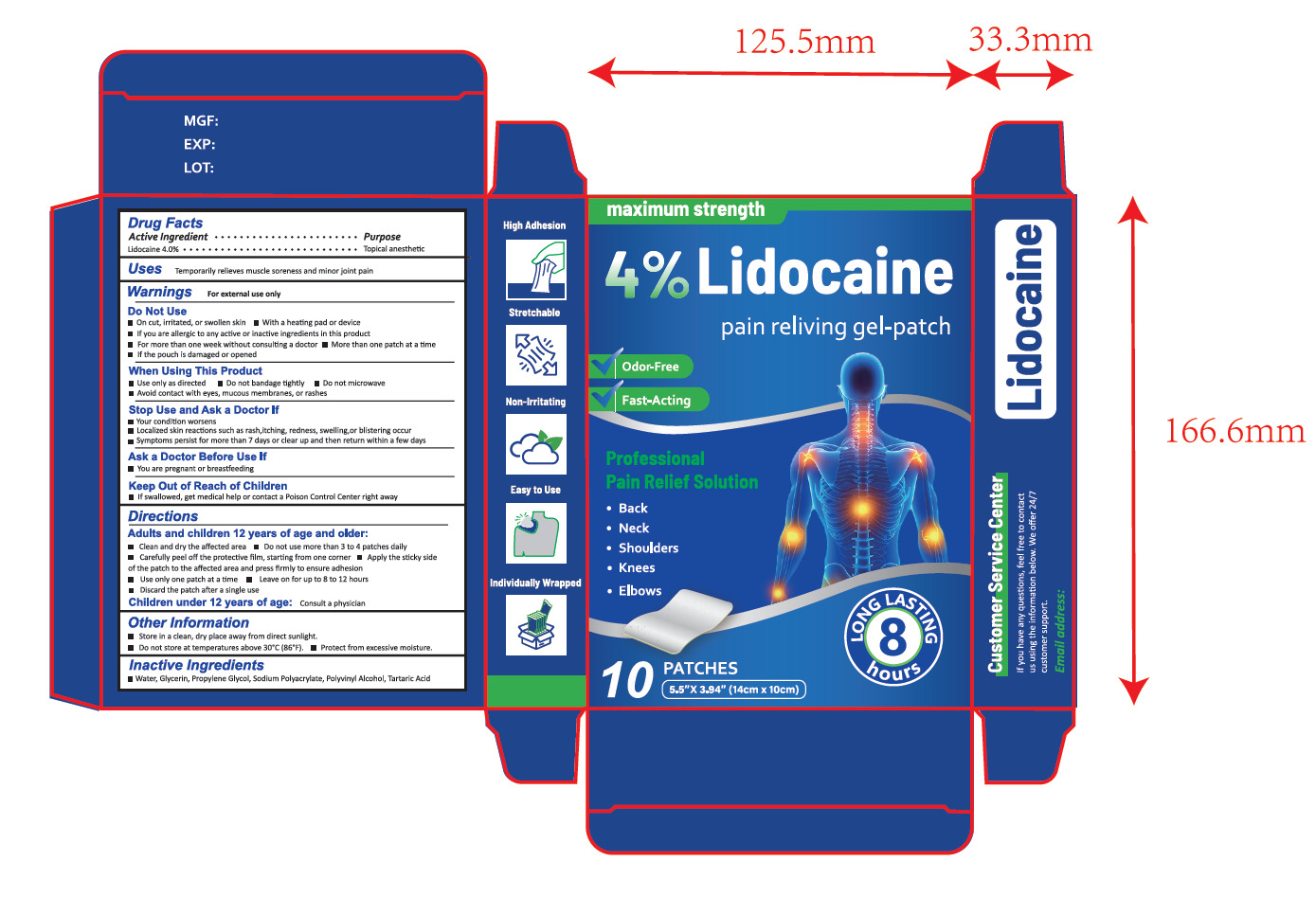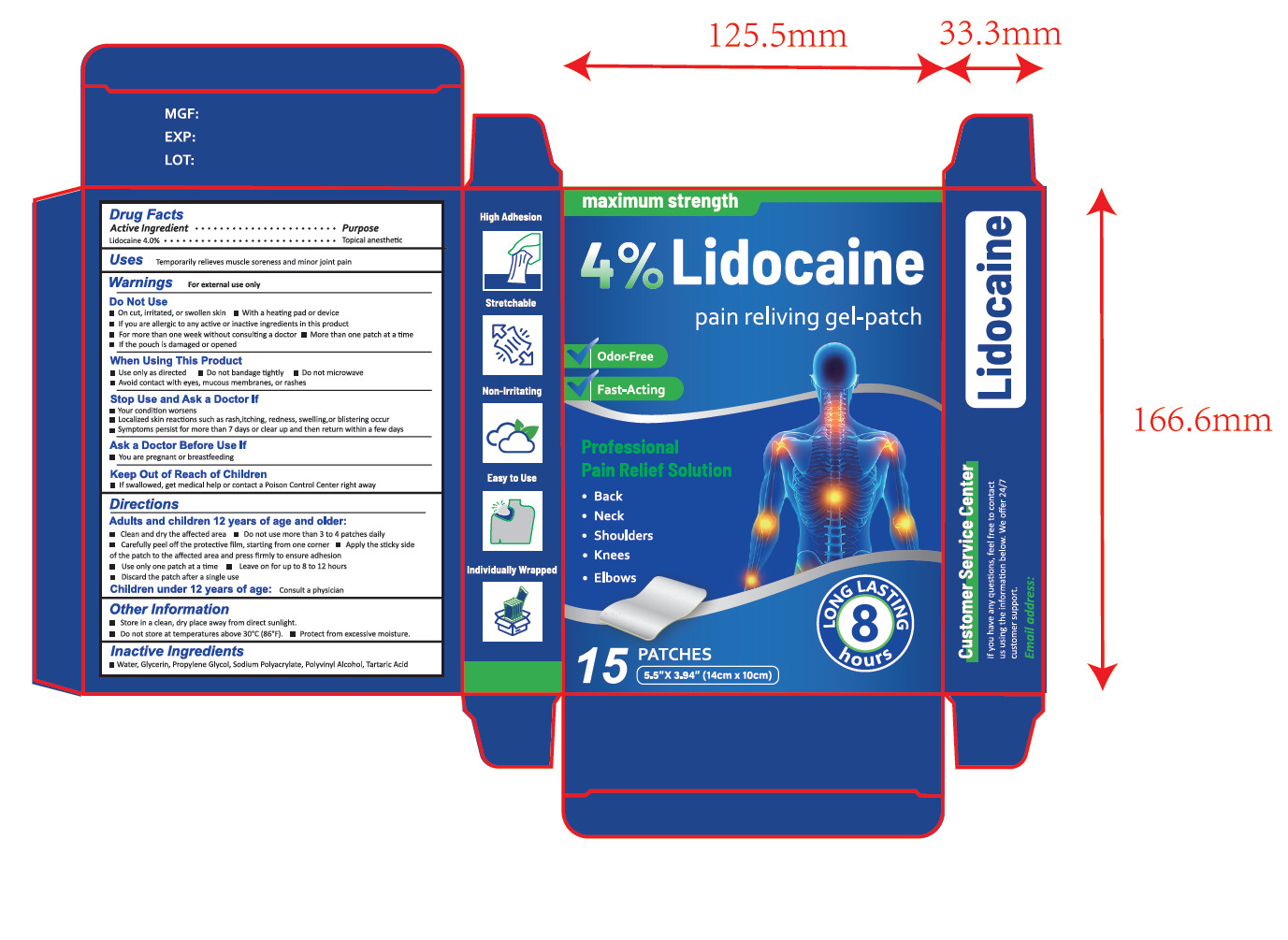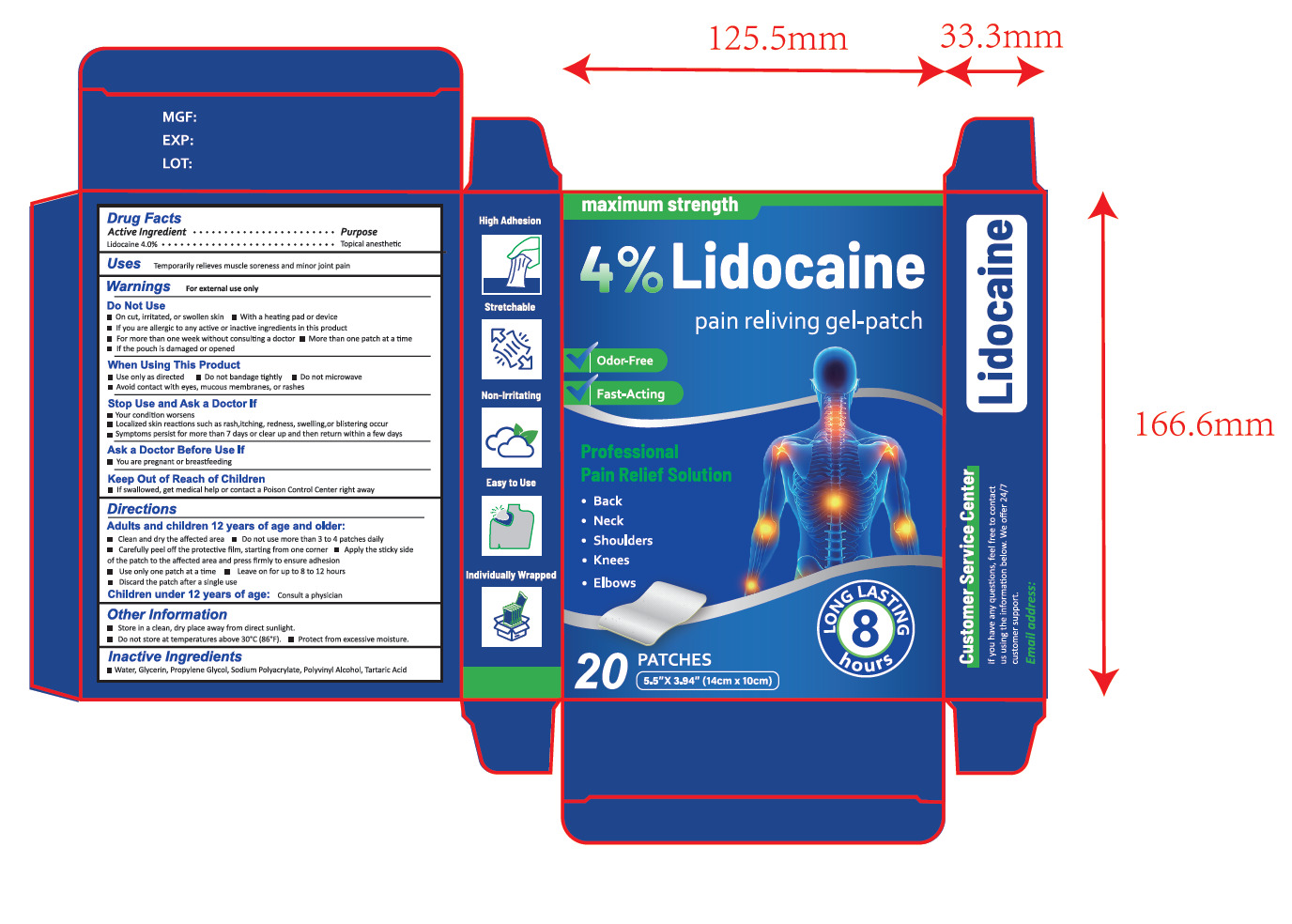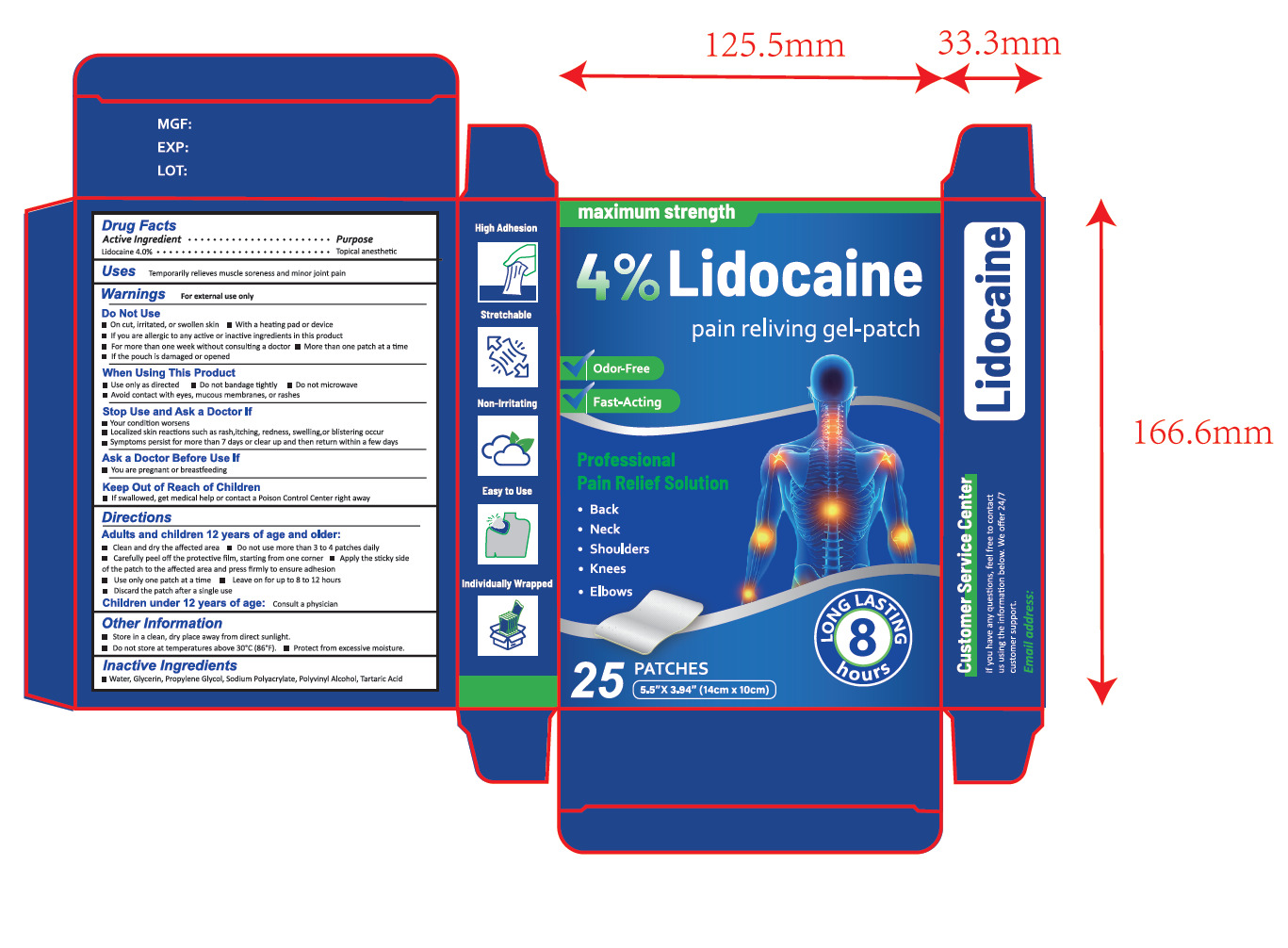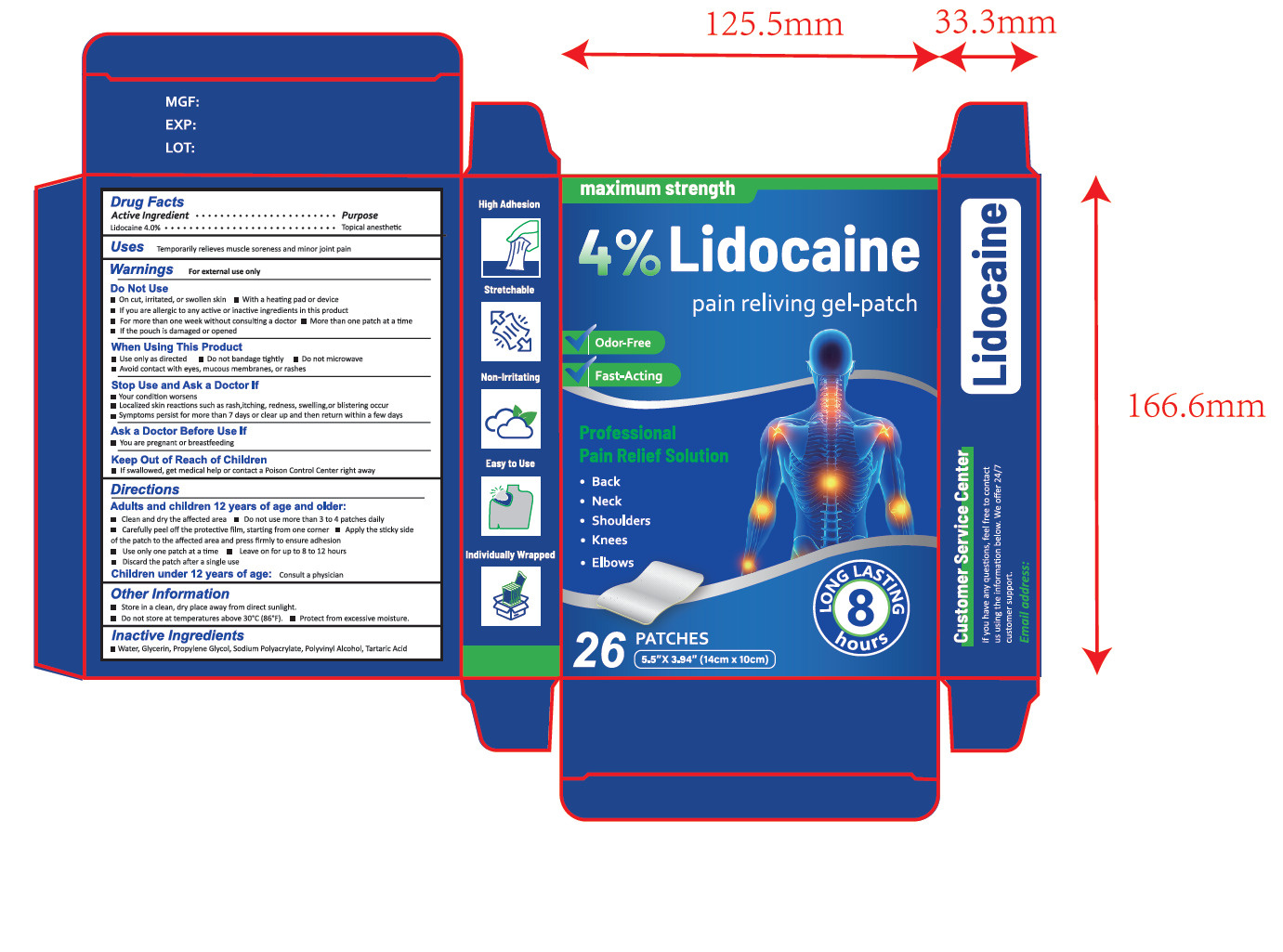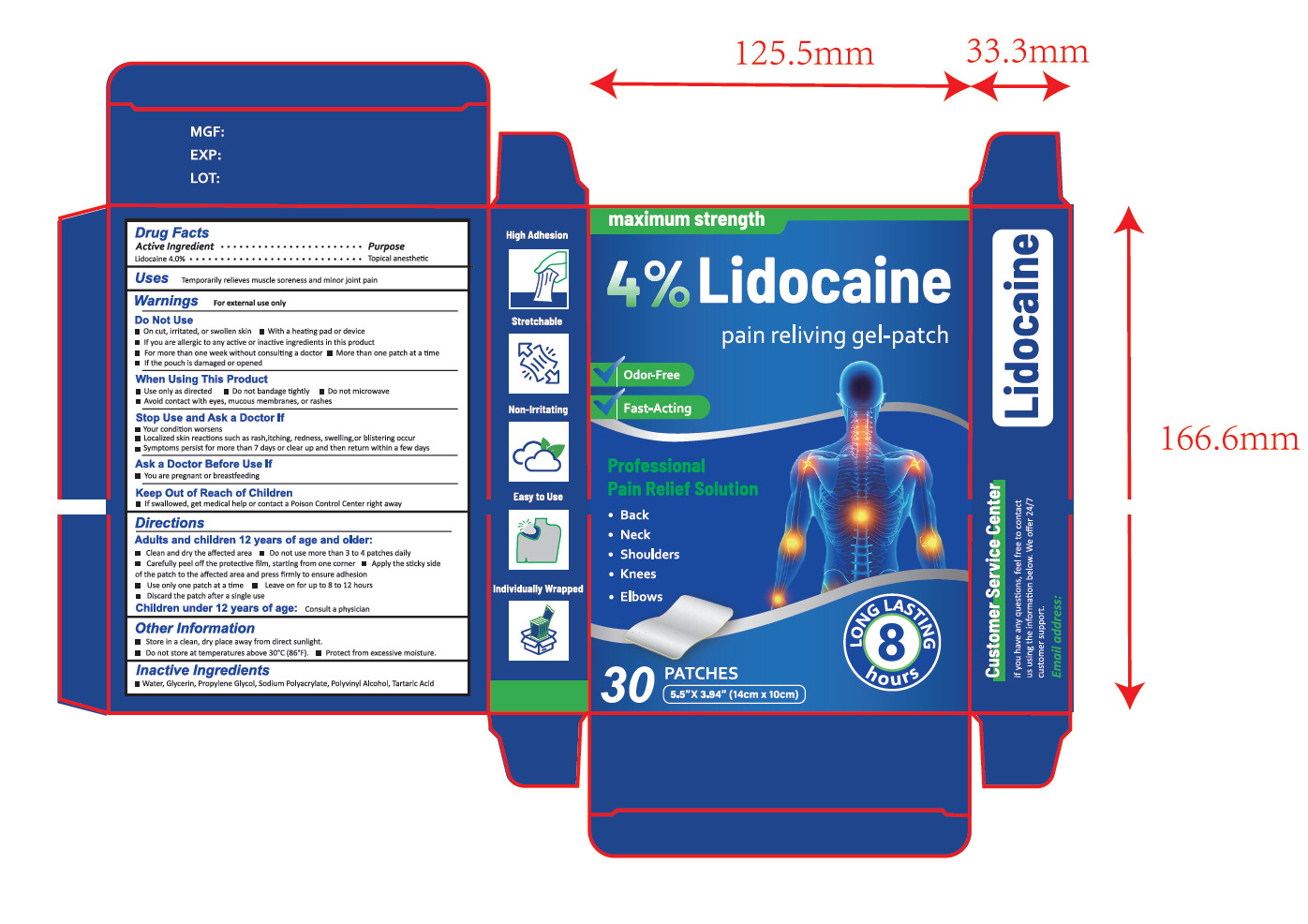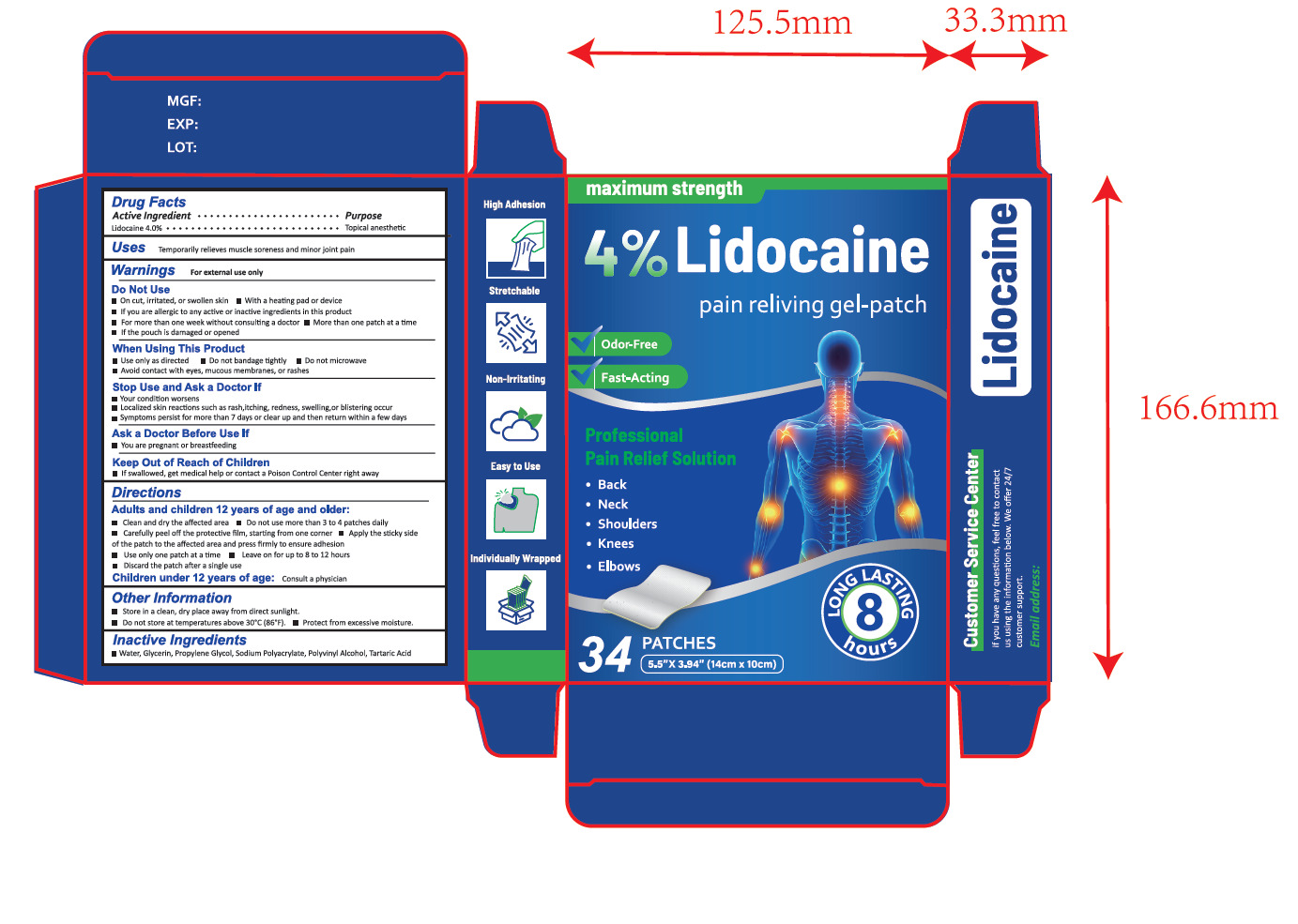 DRUG LABEL: LidocainePain pain reliving gel-patch
NDC: 84291-005 | Form: PATCH
Manufacturer: Shenzhen Yuetai Electronic Commerce Co., Ltd
Category: otc | Type: HUMAN OTC DRUG LABEL
Date: 20251216

ACTIVE INGREDIENTS: LIDOCAINE 4 U/100 U
INACTIVE INGREDIENTS: WATER; GLYCERIN; PROPYLENE GLYCOL; SODIUM POLYACRYLATE (2500000 MW); POLYVINYL ALCOHOL; TARTARIC ACID

84291-005

Active Ingredient(s)

Lidocaine 4.0%

Purpose

Topical anesthetic

Use

Temporarily relieves muscle soreness and minor joint pain

Warnings

For external use only

Do not use

■On cut, irritated, or swollen skin ■ With a heating pad or device
■If you are allergic to any active or inactive ingredients in this product
■For more than one week without consulting a doctor ■More than one patch at a time
■If the pouch is damaged or opened

WHEN USING

Use only as directed
Do not bandage tightly
Do not microwave
Avoid contact with eyes, mucous membranes, or rashes

STOP USE

Your condition worsens
Localized skin reactions such as rash,itching, redness, swelling,or blistering occur
Symptoms persist for more than 7 days or clear up and then return within a few days

KEEP OUT OF REACH OF CHILDREN

If swallowed, get medical help or contact a Poison Control Center right away

Directions

Adults and children 12 years of age and older:
■ Clean and dry the affected area
■ Do not use more than 3 to 4 patches daily
■ Carefully peel off the protective film, starting from one corner

■ Apply the sticky side of the patch to the affected area and press firmly to ensure adhesion
■ Use only one patch at a time

■ Leave on for up to 8 to 12 hours
■ Discard the patch after a single use
Children under 12 years of age:Consult a physician

Other information

Store in a clean, dry place away from direct sunlight.
Do not store at temperatures above 30°C (86°F).
Protect from excessive moisture..

Inactive ingredients

Water, Glycerin, Propylene Glycol, Sodium Polyacrylate, Polyvinyl Alcohol, Tartaric Acid